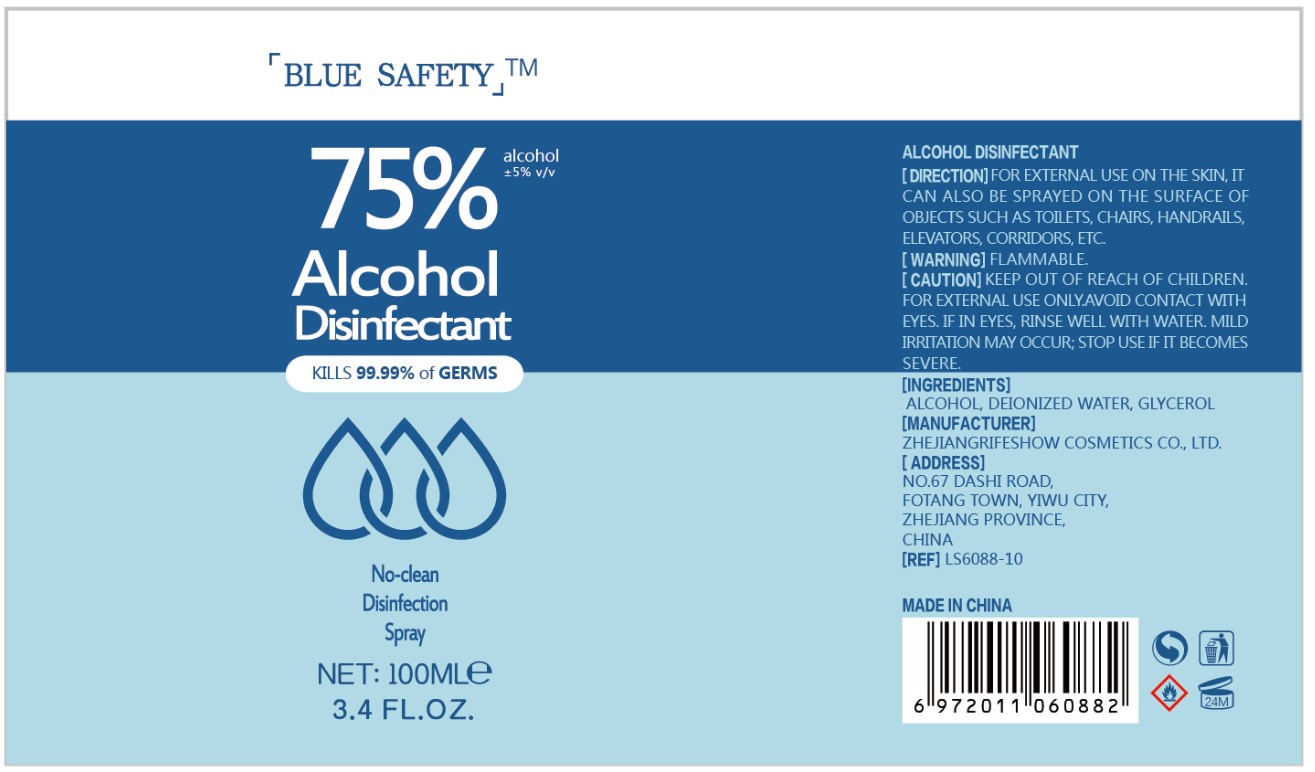 DRUG LABEL: alcohol disinfectant
NDC: 56084-016 | Form: LIQUID
Manufacturer: ZHEJIANG RIFESHOW COSMETICS CO.,LTD
Category: otc | Type: HUMAN OTC DRUG LABEL
Date: 20200602

ACTIVE INGREDIENTS: ALCOHOL 75 mL/100 mL
INACTIVE INGREDIENTS: GLYCERIN 1.45 mL/100 mL; WATER

Alcohol disinfectant

Active Ingredient(s)

Alcohol 75%±5% v/v. Purpose: kill 99.99% of germs

Purpose

kill 99.99% of germs

Use

Hand Sanitizer to help reduce bacteria that potentially can cause disease. For use when soap and water are not available.

Warnings

Flammable

Do not use

avoid contact with eyes,if in eyes,rinse well with water.

keep out of reach of children.for external use only,avoid contact with eyes.if in eyes,rinse well with water.mild irritation may occur;stop use if it becomes severe

STOP USE

mild irraitation may occur;Stop use if becomes severe

Keep out of reach of children.

Directions

for external use on the skin,it can also be sprayed on the surface of objects such sa toilets chairs handrails,elevator,corridors etc.

Inactive ingredients

deionized water,glycerol,